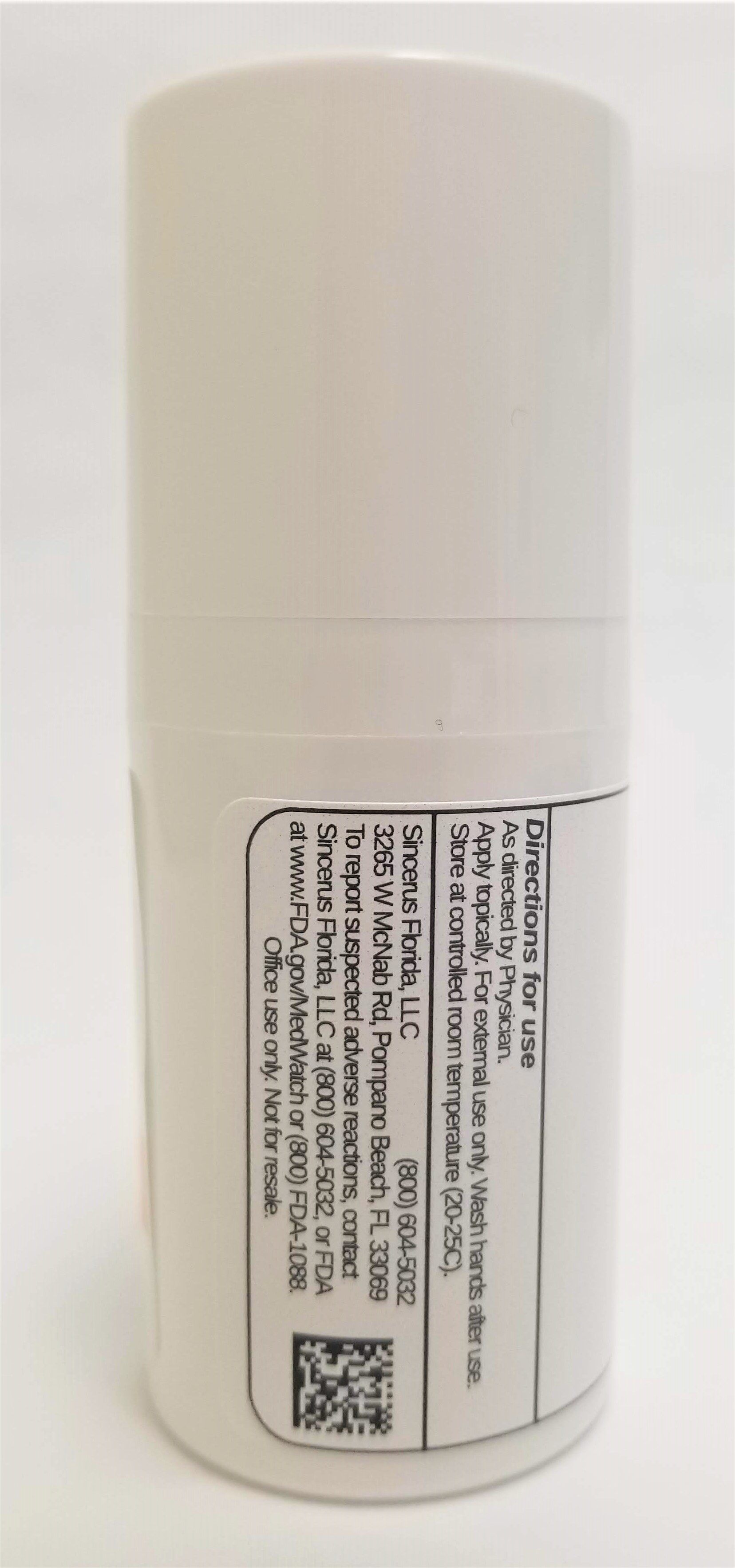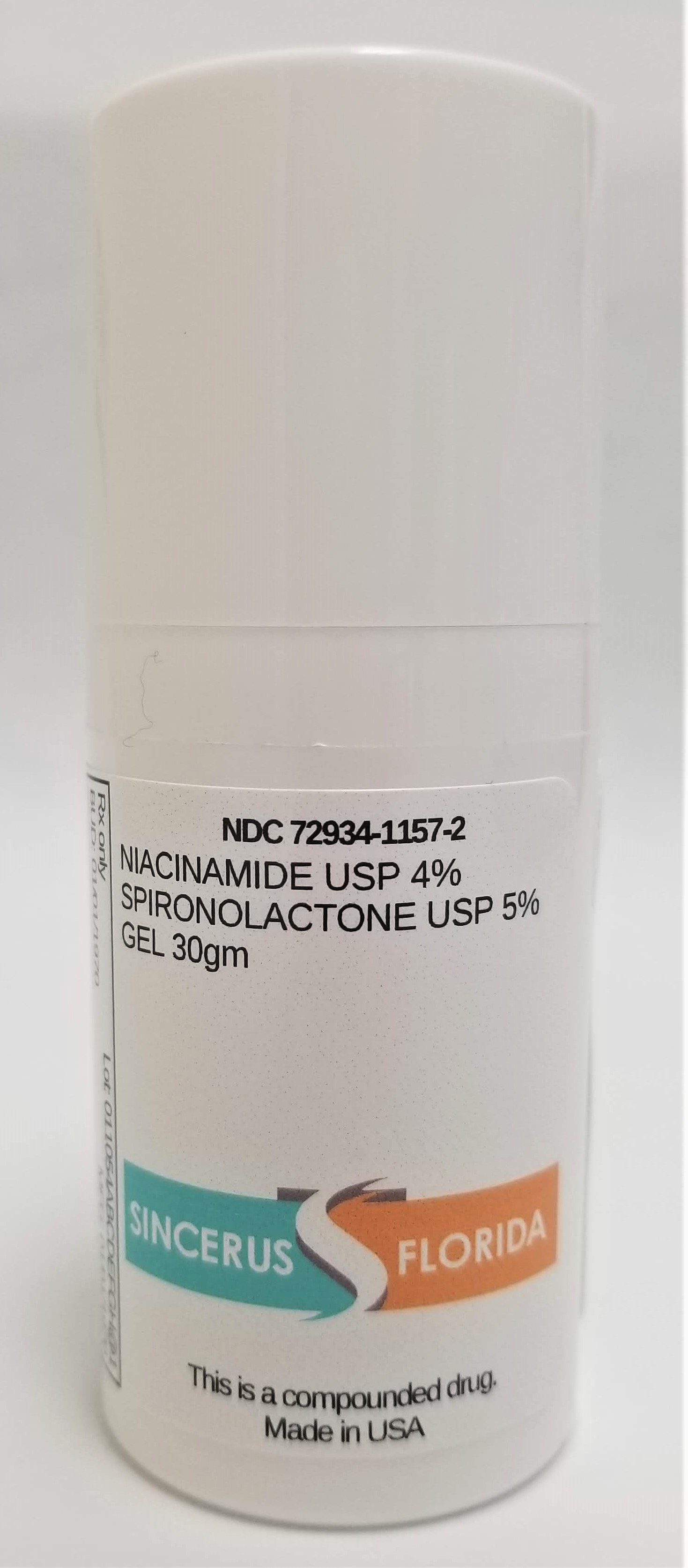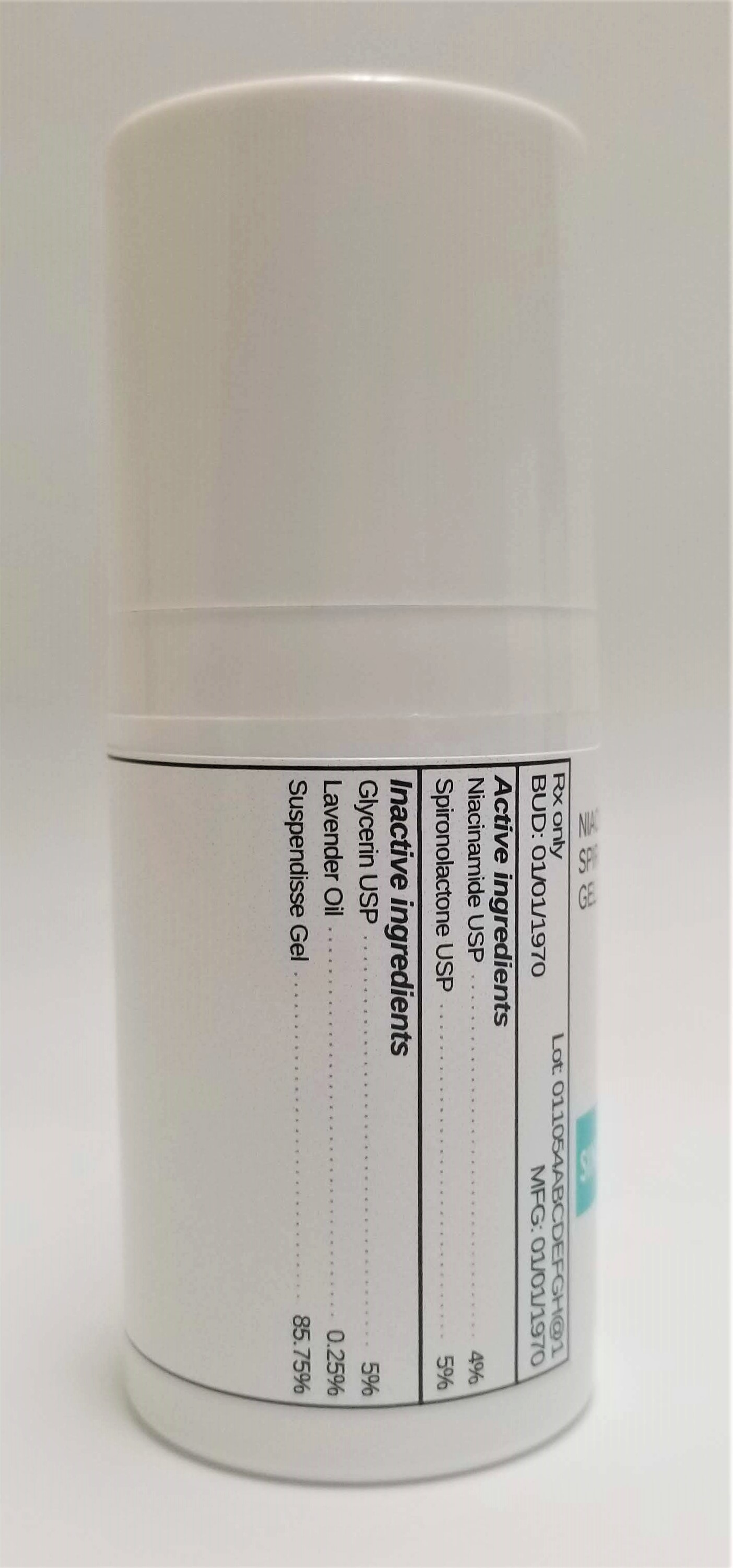 DRUG LABEL: NIACINAMIDE 4% / SPIRONOLACTONE 5%
NDC: 72934-1157 | Form: GEL
Manufacturer: Sincerus Florida, LLC
Category: prescription | Type: HUMAN PRESCRIPTION DRUG LABEL
Date: 20190509

ACTIVE INGREDIENTS: NIACINAMIDE 4 g/100 g; SPIRONOLACTONE 5 g/100 g

NIACINAMIDE 4% / SPIRONOLACTONE 5%